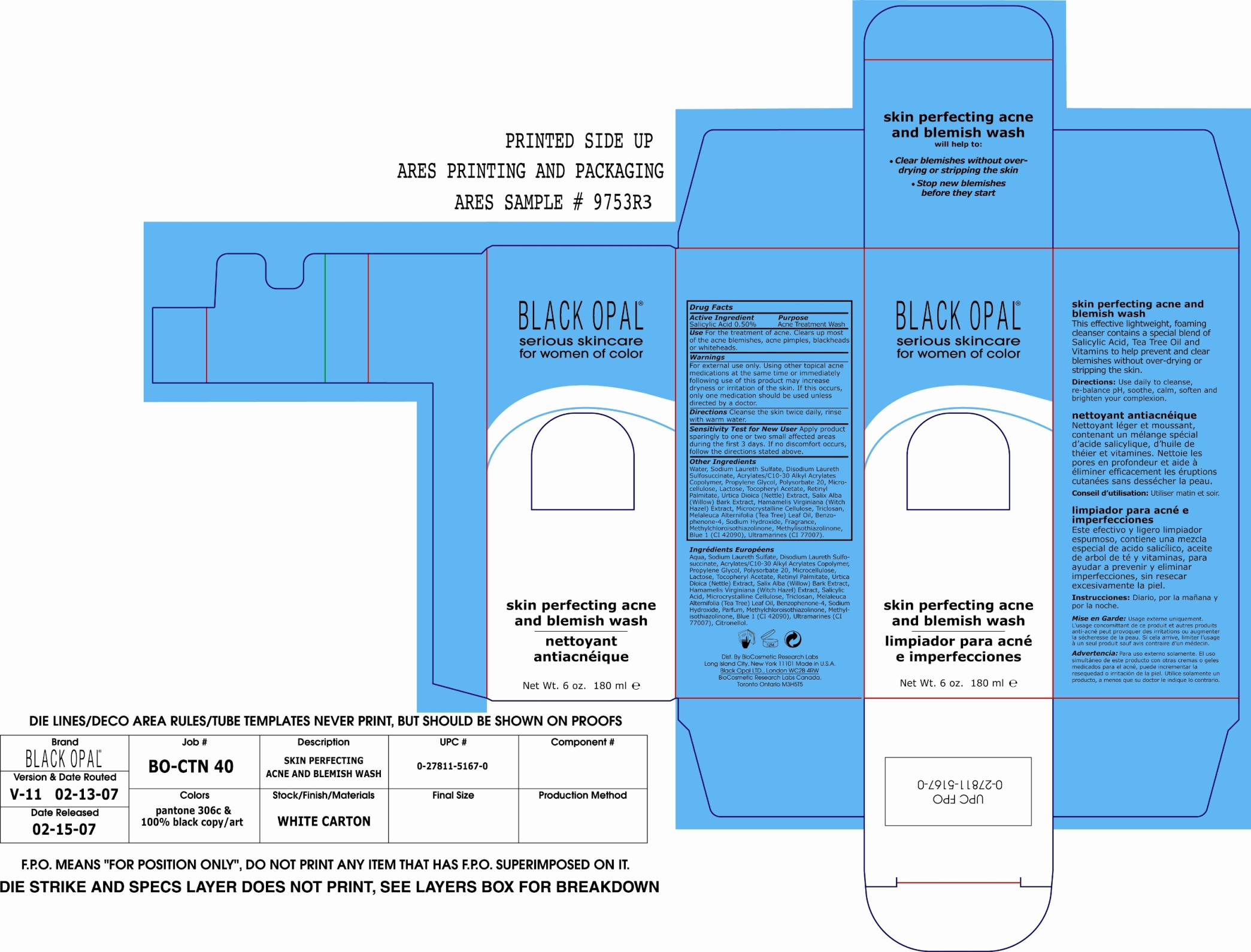 DRUG LABEL: Skin Perfecting Acne and Blemish Wash
NDC: 59735-314 | Form: RINSE
Manufacturer: Biocosmetics Research Labs
Category: otc | Type: HUMAN OTC DRUG LABEL
Date: 20060619

ACTIVE INGREDIENTS: Salicylic Acid 0.50 mL/100 mL

Skin Perfecting Acne and Blemish Wash

Active Ingredient:

Salicylic Acid 0.50%

Purpose:

Acne Treatment Wash

Use:

For the treatment of acne. Clears up most of the acne blemishes, acne pimples, blackheads and whiteheads.

Warnings:

For external use only.

Using other topical acne medications at the same time or immediately following use of this product may increase dryness or irritation of the skin. If this occurs, only one medication should be used unless directed by a doctor.

Directions:

Cleanse the skin twice daily, rinse with warm water.

PRECAUTIONS

Sensitivity test for new user:

Apply product sparingly to one or two small affected areas during the first 3 days. If no discomfort occurs, follow the directions stated above.

INACTIVE INGREDIENT

Other Ingredients:

Water, Sodium Laureth Sulfate, Disodium Laureth Sulfosuccinate, Acrylates/C10-30 Alkyl Acrylates Copolymer, Propylene Gylcol, Polysorbate 20, Microcellulose, Lactose, Tocopheryl Acetate, Retinyl Palmitate, Urtica Dioica (Nettle) Extract, Salix Alba (Willow) Bark Extract, Hamamelis Virginiana (Witch Hazel) Extract, Microcrystalline Cellulose, Triclosan, Melaleuca Alternifolia (Tea Tree) Leaf Oil, Benzophenone-4, Sodium hydroxide, Fragrance, Methylchloroisothiazolinone, Methylisothiazolinone, Blue 1 (CI 42090), Ultramarines (CI 77007).